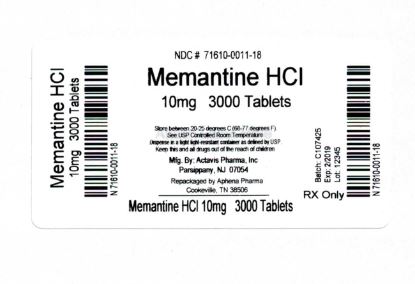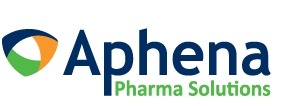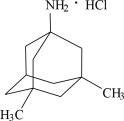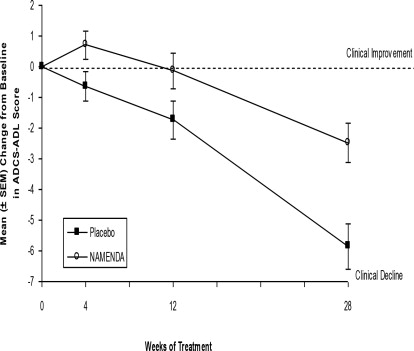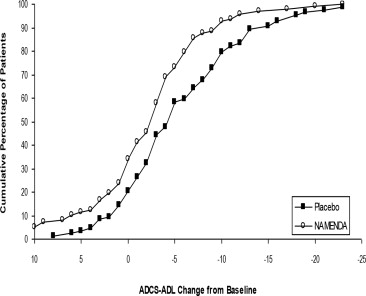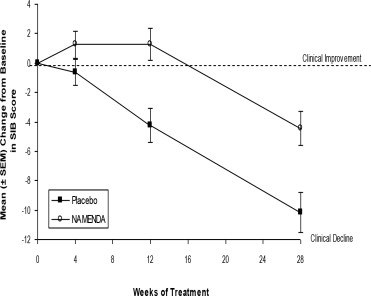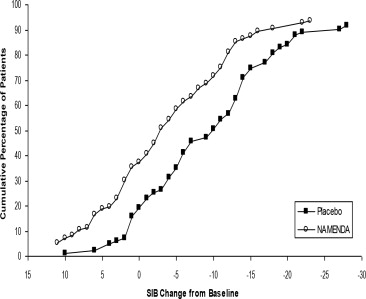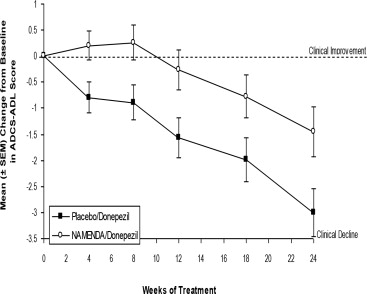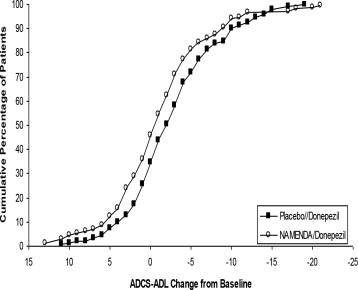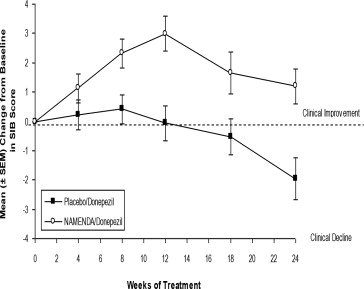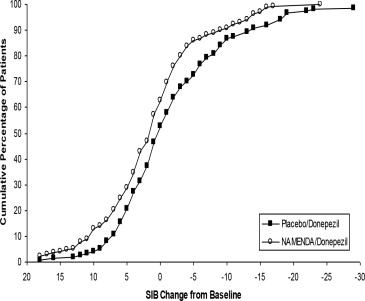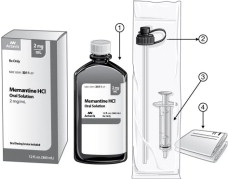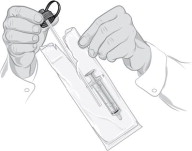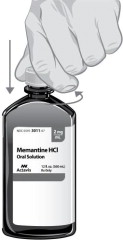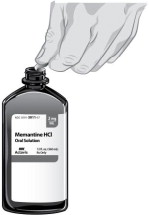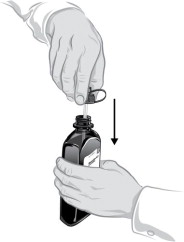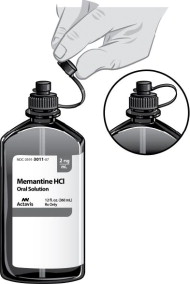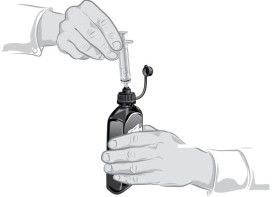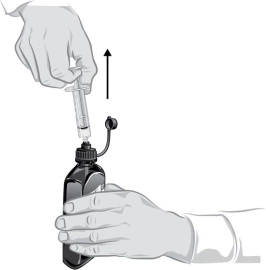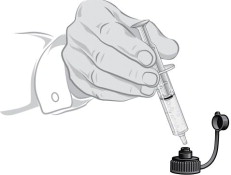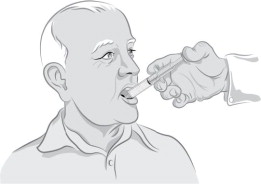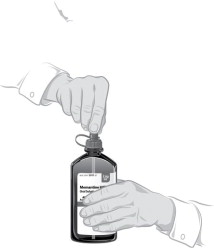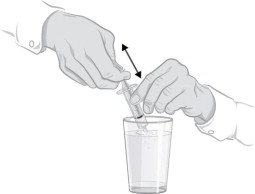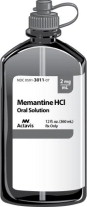 DRUG LABEL: memantine hydrochloride
NDC: 71610-011 | Form: TABLET
Manufacturer: Aphena Pharma Solutions - Tennessee, LLC
Category: prescription | Type: HUMAN PRESCRIPTION DRUG LABEL
Date: 20171130

ACTIVE INGREDIENTS: MEMANTINE HYDROCHLORIDE 10 mg/1 1
INACTIVE INGREDIENTS: hypromelloses; titanium dioxide; polyethylene glycol 400; ferrosoferric oxide

HIGHLIGHTS OF PRESCRIBING INFORMATION

These highlights do not include all the information needed to use Memantine HCl safely and effectively. See full prescribing information for Memantine HCl.
Memantine HCl tablets, for oral use
Memantine HCl solution, for oral use
Initial U.S. Approval: 2003

1 INDICATIONS AND USAGE

Memantine HCl is an N-methyl-D-aspartate (NMDA) receptor antagonist indicated for the treatment of moderate to severe dementia of the Alzheimer's type. (1)

2 DOSAGE AND ADMINISTRATION

- May be taken with or without food (2)
- Initial dose is 5 mg once daily. Increase dose in 5 mg increments to a maintenance dose of 10 mg twice daily. A minimum of 1 week of treatment with the previous dose should be observed before increasing the dose. (2)
- Severe renal impairment: recommended dose is 5 mg twice daily. (2)

3 DOSAGE FORMS AND STRENGTHS

- Tablets: 5 mg and 10 mg (3)
- Oral Solution: 2 mg/mL (3)

4 CONTRAINDICATIONS

- Memantine HCl is contraindicated in patients with known hypersensitivity to memantine hydrochloride or to any excipients used in the formulation. (4)

5 WARNINGS AND PRECAUTIONS

- Conditions that raise urine pH may decrease the urinary elimination of memantine, resulting in increased plasma levels of memantine. (5.1, 7.1)

6 ADVERSE REACTIONS

Most common adverse reactions (≥ 5 % and greater than placebo) are dizziness, headache, confusion and constipation. (6.1)

To report SUSPECTED ADVERSE REACTIONS, contact Actavis at 1-800-272-5525 or FDA at 1-800-FDA-1088 or www.fda.gov/medwatch.

FULL PRESCRIBING INFORMATION

1 INDICATIONS AND USAGE

Memantine hydrochloride is indicated for the treatment of moderate to severe dementia of the Alzheimer's type.

2 DOSAGE AND ADMINISTRATION

The recommended starting dose of Memantine HCl is 5 mg once daily. The dose should be increased in 5 mg increments to 10 mg/day (5 mg twice daily), 15 mg/day (5 mg and 10 mg as separate doses), and 20 mg/day (10 mg twice daily). The minimum recommended interval between dose increases is one week. The dosage shown to be effective in controlled clinical trials is 20 mg/day.

Memantine HCl can be taken with or without food. If a patient misses a single dose of Memantine HCl, that patient should not double up on the next dose. The next dose should be taken as scheduled.

If a patient fails to take Memantine HCl for several days, dosing may need to be resumed at lower doses and retitrated as described above.

Do not mix Memantine HCl oral solution with any other liquid. The oral solution is administered with a dosing device that comes with the drug and consists of a syringe, syringe adaptor cap, tubing and other supplies a patient needs to administer the drug. The supplied syringe should be used to withdraw the correct volume of oral solution and the oral solution should be slowly squirted into the corner of the patient's mouth.

Special Populations

Renal Impairment

A target dose of 5 mg twice daily is recommended in patients with severe renal impairment (creatinine clearance of 5 – 29 mL/min based on the Cockroft-Gault equation).

Hepatic Impairment

Memantine HCl should be administered with caution to patients with severe hepatic impairment [see Clinical Pharmacology (12.3)].

3 DOSAGE FORMS AND STRENGTHS

Memantine HCl 5 mg tablet: capsule-shaped, film-coated tablets are tan, with the strength (5) debossed on one side and FL on the other.

Memantine HCl 10 mg tablet: capsule-shaped, film-coated tablets are gray, with the strength (10) debossed on one side and FL on the other.

Memantine HCl 2 mg/mL oral solution: clear, alcohol-free, sugar-free, and peppermint flavored.

4 CONTRAINDICATIONS

Memantine hydrochloride is contraindicated in patients with known hypersensitivity to memantine hydrochloride or to any excipients used in the formulation.

5 WARNINGS AND PRECAUTIONS

5.1 Genitourinary Conditions

Conditions that raise urine pH may decrease the urinary elimination of memantine resulting in increased plasma levels of memantine [see Drug Interactions (7.1)].

6 ADVERSE REACTIONS

6.1 Clinical Trials Experience

Memantine HCl was evaluated in eight double-blind placebo-controlled trials involving a total of 1862 dementia (Alzheimer's disease, vascular dementia) patients (940 patients treated with Memantine HCl and 922 patients treated with placebo) for a treatment period up to 28 weeks.

Because clinical trials are conducted under widely varying conditions, adverse reaction rates observed in the clinical trials of a drug cannot be directly compared to rates in the clinical trials of another drug and may not reflect the rates observed in clinical practice.

Adverse Events Leading to Discontinuation

In placebo-controlled trials in which dementia patients received doses of Memantine HCl up to 20 mg/day, the likelihood of discontinuation because of an adverse reaction was the same in the Memantine HCl group (10.1%) as in the placebo group (11.5%). No individual adverse reaction was associated with the discontinuation of treatment in 1% or more of Memantine HCl-treated patients and at a rate greater than placebo.

Most Common Adverse Reactions

In double-blind placebo-controlled trials involving dementia patients, the most common adverse reactions (incidence ≥ 5% and higher than placebo) in patients treated with Memantine HCl were dizziness, headache, confusion and constipation. Table 1 lists all adverse reactions that occurred in at least 2% of patients treated with Memantine HCl and at an incidence greater than placebo.

Table 1: Adverse Reactions Reported in Controlled Clinical Trials in at Least 2% of Patients Receiving Memantine HCl and at a Higher Frequency than Placebo-treated Patients
Adverse Reaction | Placebo (N = 922) % | Memantine HCl (N = 940) %
Body as a Whole
Fatigue | 1 | 2
Pain | 1 | 3
Cardiovascular System
Hypertension | 2 | 4
Central and Peripheral Nervous System
Dizziness | 5 | 7
Headache | 3 | 6
Gastrointestinal System
Constipation | 3 | 5
Vomiting | 2 | 3
Musculoskeletal System
Back pain | 2 | 3
Psychiatric Disorders
Confusion | 5 | 6
Somnolence | 2 | 3
Hallucination | 2 | 3
Respiratory System
Coughing | 3 | 4
Dyspnea | 1 | 2

The overall profile of adverse reactions and the incidence rates for individual adverse reactions in the subpopulation of patients with moderate to severe Alzheimer's disease were not different from the profile and incidence rates described above for the overall dementia population.

Seizures

Memantine HCl has not been systematically evaluated in patients with a seizure disorder. In clinical trials of Memantine HCl, seizures occurred in 0.2% of patients treated with Memantine HCl and 0.5% of patients treated with placebo.

6.2 Postmarketing Experience

The following adverse reactions have been identified during post-approval use of memantine.

Because these reactions are reported voluntarily from a population of uncertain size, it is not always possible to reliably estimate their frequency or establish a causal relationship to drug exposure. These reactions include:

Blood and Lymphatic System Disorders - agranulocytosis, leukopenia (including neutropenia), pancytopenia, thrombocytopenia, thrombotic thrombocytopenic purpura.

Cardiac Disorders - cardiac failure congestive.

Gastrointestinal Disorders - pancreatitis.

Hepatobiliary Disorders – hepatitis.

Psychiatric Disorders - suicidal ideation.

Renal and Urinary Disorders - acute renal failure (including increased creatinine and renal insufficiency).

Skin Disorders - Stevens Johnson syndrome.

7 DRUG INTERACTIONS

7.1 Drugs that Make the Urine Alkaline

The clearance of memantine was reduced by about 80% under alkaline urine conditions at pH 8. Therefore, alterations of urine pH towards the alkaline condition may lead to an accumulation of the drug with a possible increase in adverse effects. Urine pH is altered by diet, drugs (e.g. carbonic anhydrase inhibitors, sodium bicarbonate) and clinical state of the patient (e.g. renal tubular acidosis or severe infections of the urinary tract). Hence, memantine should be used with caution under these conditions.

7.2 Use with Other N-methyl-D-aspartate (NMDA) Antagonists

The combined use of Memantine HCl with other NMDA antagonists (amantadine, ketamine, and dextromethorphan) has not been systematically evaluated and such use should be approached with caution.

8 USE IN SPECIFIC POPULATIONS

8.1 Pregnancy

Pregnancy Category B

There are no adequate and well-controlled studies of memantine in pregnant women. Memantine HCl should be used during pregnancy only if the potential benefit justifies the potential risk to the fetus.

Memantine given orally to pregnant rats and pregnant rabbits during the period of organogenesis was not teratogenic up to the highest doses tested (18 mg/kg/day in rats and 30 mg/kg/day in rabbits, which are 9 and 30 times, respectively, the maximum recommended human dose [MRHD] on a mg/m^2 basis).

Slight maternal toxicity, decreased pup weights and an increased incidence of non-ossified cervical vertebrae were seen at an oral dose of 18 mg/kg/day in a study in which rats were given oral memantine beginning pre-mating and continuing through the postpartum period. Slight maternal toxicity and decreased pup weights were also seen at this dose in a study in which rats were treated from day 15 of gestation through the postpartum period. The no-effect dose for these effects was 6 mg/kg, which is 3 times the MRHD on a mg/m^2 basis.

8.3 Nursing Mothers

It is not known whether this drug is excreted in human milk. Because many drugs are excreted in human milk, caution should be exercised when Memantine HCl is administered to a nursing mother.

8.4 Pediatric Use

Safety and effectiveness in pediatric patients have not been established.

8.5 Geriatric Use

The majority of people with Alzheimer's disease are 65 years and older. In the clinical studies of Memantine HCl the mean age of patients was approximately 76; over 90% of patients were 65 years and older, 60% were 75 years and older, and 12% were at or above 85 years of age. The efficacy and safety data presented in the clinical trial sections were obtained from these patients. There were no clinically meaningful differences in most adverse events reported by patient groups ≥65 years old and <65 year old.

8.6 Renal Impairment

No dosage adjustment is needed in patients with mild or moderate renal impairment. A dosage reduction is recommended in patients with severe renal impairment [see Dosage and Administration (2) and Clinical Pharmacology (12.3)].

8.7 Hepatic Impairment

No dosage adjustment is needed in patients with mild or moderate hepatic impairment. Memantine HCl should be administered with caution to patients with severe hepatic impairment [see Dosage and Administration (2) and Clinical Pharmacology (12.3)].

10 OVERDOSAGE

Signs and symptoms most often accompanying memantine overdosage in clinical trials and from worldwide marketing experience, alone or in combination with other drugs and/or alcohol, include agitation, asthenia, bradycardia, confusion, coma, dizziness, ECG changes, increased blood pressure, lethargy, loss of consciousness, psychosis, restlessness, slowed movement, somnolence, stupor, unsteady gait, visual hallucinations, vertigo, vomiting, and weakness. The largest known ingestion of memantine worldwide was 2.0 grams in a patient who took memantine in conjunction with unspecified antidiabetic medications. The patient experienced coma, diplopia, and agitation, but subsequently recovered. Fatal outcome has been very rarely reported with memantine, and the relationship to memantine was unclear.

Because strategies for the management of overdose are continually evolving, it is advisable to contact a poison control center to determine the latest recommendations for the management of an overdose of any drug. As in any cases of overdose, general supportive measures should be utilized, and treatment should be symptomatic. Elimination of memantine can be enhanced by acidification of urine.

11 DESCRIPTION

Memantine hydrochloride is an orally active NMDA receptor antagonist. The chemical name for memantine hydrochloride is 1-amino-3,5-dimethyladamantane hydrochloride with the following structural formula:

The molecular formula is C12H21N•HCl and the molecular weight is 215.76. Memantine HCl occurs as a fine white to off-white powder and is soluble in water.

Memantine HCl is available as tablets or as an oral solution. Memantine HCl is available for oral administration as capsule-shaped, film-coated tablets containing 5 mg and 10 mg of memantine hydrochloride. The tablets also contain the following inactive ingredients: microcrystalline cellulose/colloidal silicon dioxide, talc, croscarmellose sodium, and magnesium stearate. In addition the following inactive ingredients are also present as components of the film coat: hypromellose, titanium dioxide, polyethylene glycol 400, FD&C yellow #6 and FD&C blue #2 (5 mg tablets), and hypromellose, titanium dioxide, macrogol/polyethylene glycol 400 and iron oxide black (10 mg tablets). Memantine HCl oral solution contains memantine hydrochloride in a strength equivalent to 2 mg of memantine hydrochloride in each mL. The oral solution also contains the following inactive ingredients: sorbitol solution (70%), methylparaben, propylparaben, propylene glycol, glycerin, natural peppermint flavor #104, citric acid, sodium citrate, and purified water.

12 CLINICAL PHARMACOLOGY

12.1 Mechanism of Action

Persistent activation of central nervous system N-methyl-D-aspartate (NMDA) receptors by the excitatory amino acid glutamate has been hypothesized to contribute to the symptomatology of Alzheimer's disease. Memantine is postulated to exert its therapeutic effect through its action as a low to moderate affinity uncompetitive (open-channel) NMDA receptor antagonist which binds preferentially to the NMDA receptor-operated cation channels. There is no evidence that memantine prevents or slows neurodegeneration in patients with Alzheimer's disease.

12.2 Pharmacodynamics

Memantine showed low to negligible affinity for GABA, benzodiazepine, dopamine, adrenergic, histamine and glycine receptors and for voltage-dependent Ca^2+, Na^+ or K^+ channels. Memantine also showed antagonistic effects at the 5HT3 receptor with a potency similar to that for the NMDA receptor and blocked nicotinic acetylcholine receptors with one-sixth to one-tenth the potency.

In vitro studies have shown that memantine does not affect the reversible inhibition of acetylcholinesterase by donepezil, galantamine, or tacrine.

12.3 Pharmacokinetics

Absorption

Following oral administration memantine is highly absorbed with peak concentrations reached in about 3-7 hours. Memantine has linear pharmacokinetics over the therapeutic dose range. Food has no effect on the absorption of memantine.

Distribution

The mean volume of distribution of memantine is 9-11 L/kg and the plasma protein binding is low (45%).

Metabolism

Memantine undergoes partial hepatic metabolism. The hepatic microsomal CYP450 enzyme system does not play a significant role in the metabolism of memantine.

Elimination

Memantine is excreted predominantly (about 48%) unchanged in urine and has a terminal elimination half- life of about 60-80 hours.

The remainder is converted primarily to three polar metabolites which possess minimal NMDA receptor antagonistic activity: the N-glucuronide conjugate, 6-hydroxy memantine, and 1-nitroso-deaminated memantine. A total of 74% of the administered dose is excreted as the sum of the parent drug and the N-glucuronide conjugate. Renal clearance involves active tubular secretion moderated by pH dependent tubular reabsorption.

Pharmacokinetics in Specific Populations

Gender

Following multiple dose administration of Memantine HCl 20 mg daily, females had about 45% higher exposure than males, but there was no difference in exposure when body weight was taken into account.

Elderly

The pharmacokinetics of Memantine HCl in young and elderly subjects are similar.

Renal Impairment

Memantine pharmacokinetics were evaluated following single oral administration of 20 mg memantine HCl in 8 subjects with mild renal impairment (creatinine clearance, CLcr, >50 – 80 mL/min), 8 subjects with moderate renal impairment (CLcr 30 – 49 mL/min), 7 subjects with severe renal impairment (CLcr 5 – 29 mL/min) and 8 healthy subjects (CLcr > 80 mL/min) matched as closely as possible by age, weight and gender to the subjects with renal impairment. Mean AUC0-∞ increased by 4%, 60%, and 115% in subjects with mild, moderate, and severe renal impairment, respectively, compared to healthy subjects. The terminal elimination half-life increased by 18%, 41%, and 95% in subjects with mild, moderate, and severe renal impairment, respectively, compared to healthy subjects.

No dosage adjustment is recommended for patients with mild and moderate renal impairment. Dosage should be reduced in patients with severe renal impairment [see Dosage and Administration (2)].

Hepatic Impairment

Memantine pharmacokinetics were evaluated following the administration of single oral doses of 20 mg in 8 subjects with moderate hepatic impairment (Child-Pugh Class B, score 7-9) and 8 subjects who were age-, gender-, and weight-matched to the hepatically-impaired subjects. There was no change in memantine exposure (based on Cmax and AUC) in subjects with moderate hepatic impairment as compared with healthy subjects. However, terminal elimination half-life increased by about 16% in subjects with moderate hepatic impairment as compared with healthy subjects. No dose adjustment is recommended for patients with mild and moderate hepatic impairment. Memantine should be administered with caution to patients with severe hepatic impairment as the pharmacokinetics of memantine have not been evaluated in that population.

Drug-Drug Interactions

Use with Cholinesterase Inhibitors

Coadministration of memantine with the AChE inhibitor donepezil HCl did not affect the pharmacokinetics of either compound. Furthermore, memantine did not affect AChE inhibition by donepezil. In a 24-week controlled clinical study in patients with moderate to severe Alzheimer's disease, the adverse event profile observed with a combination of Memantine HCl and donepezil was similar to that of donepezil alone.

Effect of Memantine HCl on the Metabolism of Other Drugs

In vitro studies conducted with marker substrates of CYP450 enzymes (CYP1A2, -2A6, -2C9, -2D6, -2E1, -3A4) showed minimal inhibition of these enzymes by memantine. In addition, in vitro studies indicate that at concentrations exceeding those associated with efficacy, memantine does not induce the cytochrome P450 isozymes CYP1A2, -2C9, -2E1 and -3A4/5. No pharmacokinetic interactions with drugs metabolized by these enzymes are expected.

Pharmacokinetic studies evaluated the potential of memantine for interaction with warfarin, and buproprion. Memantine did not affect the pharmacokinetics of the CYP2B6 substrate buproprion or its metabolite hydroxybuproprion. Furthermore, memantine did not affect the pharmacokinetics or pharmacodynamics of warfarin as assessed by the prothrombin INR.

Effect of Other Drugs on Memantine HCl

Memantine is predominantly renally eliminated, and drugs that are substrates and/or inhibitors of the CYP450 system are not expected to alter the metabolism of memantine.

Drugs Eliminated via Renal Mechanisms

Because memantine is eliminated in part by tubular secretion, coadministration of drugs that use the same renal cationic system, including hydrochlorothiazide (HCTZ), triamterene (TA), metformin, cimetidine, ranitidine, quinidine, and nicotine, could potentially result in altered plasma levels of both agents. However, coadministration of Memantine HCl and HCTZ/TA did not affect the bioavailability of either memantine or TA, and the bioavailability of HCTZ decreased by 20%. In addition, coadministration of memantine with the antihyperglycemic drug Glucovance® (glyburide and metformin HCl) did not affect the pharmacokinetics of memantine, metformin and glyburide. Furthermore, memantine did not modify the serum glucose lowering effect of Glucovance®, indicating the absence of a pharmacodynamic interaction.

Drugs Highly Bound to Plasma Proteins

Because the plasma protein binding of memantine is low (45%), an interaction with drugs that are highly bound to plasma proteins, such as warfarin and digoxin, is unlikely.

13 NONCLINICAL TOXICOLOGY

13.1 Carcinogenesis, Mutagenesis, Impairment of Fertility

There was no evidence of carcinogenicity in a 113-week oral study in mice at doses up to 40 mg/kg/day (10 times the maximum recommended human dose [MRHD] on a mg/m^2 basis). There was also no evidence of carcinogenicity in rats orally dosed at up to 40 mg/kg/day for 71 weeks followed by 20 mg/kg/day (20 and 10 times the MRHD on a mg/m^2 basis, respectively) through 128 weeks.

Memantine produced no evidence of genotoxic potential when evaluated in the in vitro S. typhimurium or E. coli reverse mutation assay, an in vitro chromosomal aberration test in human lymphocytes, an in vivo cytogenetics assay for chromosome damage in rats, and the in vivo mouse micronucleus assay. The results were equivocal in an in vitro gene mutation assay using Chinese hamster V79 cells.

No impairment of fertility or reproductive performance was seen in rats administered up to 18 mg/kg/day (9 times the MRHD on a mg/m^2 basis) orally from 14 days prior to mating through gestation and lactation in females, or for 60 days prior to mating in males.

13.2 Animal Toxicology and/or Pharmacology

Memantine induced neuronal lesions (vacuolation and necrosis) in the multipolar and pyramidal cells in cortical layers III and IV of the posterior cingulate and retrosplenial neocortices in rats, similar to those which are known to occur in rodents administered other NMDA receptor antagonists. Lesions were seen after a single dose of memantine. In a study in which rats were given daily oral doses of memantine for 14 days, the no-effect dose for neuronal necrosis was 6 times the maximum recommended human dose of 20 mg/day on a mg/m^2 basis

In acute and repeat-dose neurotoxicity studies in female rats, oral administration of memantine and donepezil in combination resulted in increased incidence, severity, and distribution of neurodegeneration compared with memantine alone. The no-effect levels of the combination were associated with clinically relevant plasma memantine and donepezil exposures.

The relevance of these findings to humans is unknown.

14 CLINICAL STUDIES

The effectiveness of Memantine HCl as a treatment for patients with moderate to severe Alzheimer's disease was demonstrated in 2 randomized, double-blind, placebo-controlled clinical studies (Studies 1 and 2) conducted in the United States that assessed both cognitive function and day to day function. The mean age of patients participating in these two trials was 76 with a range of 50-93 years. Approximately 66% of patients were female and 91% of patients were Caucasian. A third study (Study 3), carried out in Latvia, enrolled patients with severe dementia, but did not assess cognitive function as a planned endpoint. Study Outcome Measures: In each U.S. study, the effectiveness of Memantine HCl was determined using both an instrument designed to evaluate overall function through caregiver-related assessment, and an instrument that measures cognition. Both studies showed that patients on Memantine HCl experienced significant improvement on both measures compared to placebo.

Day-to-day function was assessed in both studies using the modified Alzheimer's disease Cooperative Study - Activities of Daily Living inventory (ADCS-ADL). The ADCS-ADL consists of a comprehensive battery of ADL questions used to measure the functional capabilities of patients. Each ADL item is rated from the highest level of independent performance to complete loss. The investigator performs the inventory by interviewing a caregiver familiar with the behavior of the patient. A subset of 19 items, including ratings of the patient's ability to eat, dress, bathe, telephone, travel, shop, and perform other household chores has been validated for the assessment of patients with moderate to severe dementia. This is the modified ADCS-ADL, which has a scoring range of 0 to 54, with the lower scores indicating greater functional impairment.

The ability of Memantine HCl to improve cognitive performance was assessed in both studies with the Severe Impairment Battery (SIB), a multi-item instrument that has been validated for the evaluation of cognitive function in patients with moderate to severe dementia. The SIB examines selected aspects of cognitive performance, including elements of attention, orientation, language, memory, visuospatial ability, construction, praxis, and social interaction. The SIB scoring range is from 0 to 100, with lower scores indicating greater cognitive impairment.

Study 1 (Twenty-Eight-Week Study)

In a study of 28 weeks duration, 252 patients with moderate to severe probable Alzheimer's disease (diagnosed by DSM-IV and NINCDS-ADRDA criteria, with Mini-Mental State Examination scores ≥ 3 and ≤ 14 and Global Deterioration Scale Stages 5-6) were randomized to Memantine HCl or placebo. For patients randomized to Memantine HCl, treatment was initiated at 5 mg once daily and increased weekly by 5 mg/day in divided doses to a dose of 20 mg/day (10 mg twice a day).

Effects on the ADCS-ADL

Figure 1 shows the time course for the change from baseline in the ADCS-ADL score for patients in the two treatment groups completing the 28 weeks of the study. At 28 weeks of treatment, the mean difference in the ADCS-ADL change scores for the Memantine HCl-treated patients compared to the patients on placebo was 3.4 units. Using an analysis based on all patients and carrying their last study observation forward (LOCF analysis), Memantine HCl treatment was statistically significantly superior to placebo.

Figure 1: Time course of the change from baseline in
ADCS-ADL score for patients completing 28 weeks of treatment.

Figure 2 shows the cumulative percentages of patients from each of the treatment groups who had attained at least the change in the ADCS-ADL shown on the X axis. The curves show that both patients assigned to Memantine HCl and placebo have a wide range of responses and generally show deterioration (a negative change in ADCS-ADL compared to baseline), but that the Memantine HCl group is more likely to show a smaller decline or an improvement. (In a cumulative distribution display, a curve for an effective treatment would be shifted to the left of the curve for placebo, while an ineffective or deleterious treatment would be superimposed upon or shifted to the right of the curve for placebo).

Figure 2: Cumulative percentage of patients completing 28 weeks of
double-blind treatment with specified changes from baseline in ADCS-ADL scores.

Effects on the SIB

Figure 3 shows the time course for the change from baseline in SIB score for the two treatment groups over the 28 weeks of the study. At 28 weeks of treatment, the mean difference in the SIB change scores for the Memantine HCl-treated patients compared to the patients on placebo was 5.7 units. Using an LOCF analysis, Memantine HCl treatment was statistically significantly superior to placebo.

Figure 3: Time course of the change from baseline in
SIB score for patients completing 28 weeks of treatment.

Figure 4 shows the cumulative percentages of patients from each treatment group who had attained at least the measure of change in SIB score shown on the X axis. The curves show that both patients assigned to Memantine HCl and placebo have a wide range of responses and generally show deterioration, but that the Memantine HCl group is more likely to show a smaller decline or an improvement.

Figure 4: Cumulative percentage of patients completing 28 weeks of
double-blind treatment with specified changes from baseline in SIB scores.

Study 2 (Twenty-Four-Week Study)

In a study of 24 weeks duration, 404 patients with moderate to severe probable Alzheimer's disease (diagnosed by NINCDS-ADRDA criteria, with Mini-Mental State Examination scores ≥ 5 and ≤ 14) who had been treated with donepezil for at least 6 months and who had been on a stable dose of donepezil for the last 3 months were randomized to Memantine HCl or placebo while still receiving donepezil. For patients randomized to Memantine HCl, treatment was initiated at 5 mg once daily and increased weekly by 5 mg/day in divided doses to a dose of 20 mg/day (10 mg twice a day).

Effects on the ADCS-ADL

Figure 5 shows the time course for the change from baseline in the ADCS-ADL score for the two treatment groups over the 24 weeks of the study. At 24 weeks of treatment, the mean difference in the ADCS-ADL change scores for the Memantine HCl/donepezil treated patients (combination therapy) compared to the patients on placebo/donepezil (monotherapy) was 1.6 units. Using an LOCF analysis, Memantine HCl/donepezil treatment was statistically significantly superior to placebo/donepezil.

Figure 5: Time course of the change from baseline in
ADCS-ADL score for patients completing 24 weeks of treatment.

Figure 6 shows the cumulative percentages of patients from each of the treatment groups who had attained at least the measure of improvement in the ADCS-ADL shown on the X axis. The curves show that both patients assigned to Memantine HCl/donepezil and placebo/donepezil have a wide range of responses and generally show deterioration, but that the Memantine HCl/donepezil group is more likely to show a smaller decline or an improvement.

Figure 6: Cumulative percentage of patients completing 24 weeks of
double-blind treatment with specified changes from baseline in ADCS-ADL scores.

Effects on the SIB

Figure 7 shows the time course for the change from baseline in SIB score for the two treatment groups over the 24 weeks of the study. At 24 weeks of treatment, the mean difference in the SIB change scores for the Memantine HCl/donepezil-treated patients compared to the patients on placebo/donepezil was 3.3 units. Using an LOCF analysis, Memantine HCl/donepezil treatment was statistically significantly superior to placebo/donepezil.

Figure 7: Time course of the change from baseline in
SIB score for patients completing 24 weeks of treatment.

Figure 8 shows the cumulative percentages of patients from each treatment group who had attained at least the measure of improvement in SIB score shown on the X axis. The curves show that both patients assigned to Memantine HCl/donepezil and placebo/donepezil have a wide range of responses, but that the Memantine HCl/donepezil group is more likely to show an improvement or a smaller decline.

Figure 8: Cumulative percentage of patients completing 24 weeks of
double-blind treatment with specified changes from baseline in SIB scores.

Study 3 (Twelve-Week Study)

In a double-blind study of 12 weeks duration, conducted in nursing homes in Latvia, 166 patients with dementia according to DSM-III-R, a Mini-Mental State Examination score of < 10, and Global Deterioration Scale staging of 5 to 7 were randomized to either Memantine HCl or placebo. For patients randomized to Memantine HCl, treatment was initiated at 5 mg once daily and increased to 10 mg once daily after 1 week. The primary efficacy measures were the care dependency subscale of the Behavioral Rating Scale for Geriatric Patients (BGP), a measure of day-to-day function, and a Clinical Global Impression of Change (CGI-C), a measure of overall clinical effect. No valid measure of cognitive function was used in this study. A statistically significant treatment difference at 12 weeks that favored Memantine HCl over placebo was seen on both primary efficacy measures. Because the patients entered were a mixture of Alzheimer's disease and vascular dementia, an attempt was made to distinguish the two groups and all patients were later designated as having either vascular dementia or Alzheimer's disease, based on their scores on the Hachinski Ischemic Scale at study entry. Only about 50% of the patients had computerized tomography of the brain. For the subset designated as having Alzheimer's disease, a statistically significant treatment effect favoring Memantine HCl over placebo at 12 weeks was seen on both the BGP and CGI-C.

16 HOW SUPPLIED/STORAGE AND HANDLING

5 mg Tablet:

Tan, capsule-shaped, film-coated tablets with “5” debossed on one side and FL on the other.

Bottle of 60 NDC #0591-3870-60
10 x 10 Unit Dose NDC #0591-3870-44

10 mg Tablet:

Gray, capsule-shaped, film-coated tablets with “10” debossed on one side and FL on the other.

Bottle of 60 NDC #0591-3875-60
10 x 10 Unit Dose NDC #0591-3875-44

Titration Pack: NDC #0591-3900-87
Blister package containing 49 tablets (28 x 5 mg and 21 x 10 mg tablets).

Oral Solution:

2 mg/mL Oral Solution (10 mg = 5 mL)
12 fl. oz. (360 mL) bottle NDC #0591-3011-07

Store Memantine HCl tablets and oral solution at 25°C (77°F); excursions permitted to 15-30°C (59-86°F) [see USP Controlled Room Temperature].

17 PATIENT COUNSELING INFORMATION

See FDA-approved patient labeling (Patient Information and Instructions for Use).

To assure safe and effective use of Memantine HCl, the following information and instructions provided in the patient information section should be discussed with patients and caregivers.

Patients/caregivers should be instructed to follow the dose titration schedule provided by their physician or healthcare professional for Memantine HCl. They should be warned not to use any tablets of Memantine HCl that are damaged or show signs of tampering.

If a patient misses a single dose of Memantine HCl, that patient should not double up on the next dose. The next dose should be taken as scheduled. If a patient fails to take Memantine HCl for several days, dosing should not be resumed without consulting that patient's healthcare professional.

Patients/caregivers should be instructed on how to use the Memantine HCl Oral Solution dosing device. They should be made aware of the patient instruction sheet that is enclosed with the product. Patients/caregivers should be instructed to address any questions on the usage of the solution to their physician or pharmacist.

Distributed by:
Actavis Pharma, Inc.
Parsippany, NJ 07054 USA

Manufactured by:
Forest Laboratories Ireland Ltd
Clonshaugh Business and Technology Park
Clonshaugh, Dublin 17, Ireland

Licensed from Merz Pharmaceuticals GmbH

© 2005-2015 Actavis

Patient Information

Memantine hydrochloride
Tablets and Oral Solution

Read this Patient Information that comes with Memantine HCl before you start taking it and each time you get a refill. There may be new information. This information does not take the place of talking to your doctor about your medical condition or your treatment.

What is Memantine HCl?

Memantine HCl is a prescription medicine used for the treatment of moderate to severe dementia in people with Alzheimer's disease. Memantine HCl belongs to a class of medicines called NMDA (N-methyl-D-aspartate) inhibitors.

It is not known if Memantine HCl is safe and effective in children.

Who should not take Memantine HCl?

Do not take Memantine HCl if you are allergic to memantine or any of the ingredients in Memantine HCl. See the end of this leaflet for a complete list of ingredients in Memantine HCl.

What should I tell my doctor before taking Memantine HCl?

Before you take Memantine HCl, tell your doctor if you:

- have or have had seizures
- have or have had problems passing urine
- have or have had bladder or kidney problems
- have liver problems
- have any other medical conditions
- are pregnant or plan to become pregnant. It is not known if Memantine HCl will harm your unborn baby.
- are breastfeeding or plan to breastfeed. It is not known if Memantine HCl passes into your breast milk. You and your doctor should decide if you will take Memantine HCl or breastfeed.

Tell your doctor about all the medicines you take, including prescription and non-prescription medicines, vitamins, and herbal supplements.

Taking Memantine HCl with certain other medicines may affect each other. Taking Memantine HCl with other medicines can cause serious side effects.

Especially tell your doctor if you take:

- other NMDA antagonists such as amantadine, ketamine, and dextromethorphan
- medicines that make your urine alkaline such as carbonic anhydrase inhibitors and sodium bicarbonate

Ask your doctor or pharmacist for a list of these medicines, if you are not sure.

Know the medicines you take. Keep a list of them to show your doctor and pharmacist when you get a new medicine.

How should I take Memantine HCl?

- See the step-by-step instructions for taking Memantine HCl Oral Solution at the end of this Patient Information.
- Your doctor will tell you how much Memantine HCl to take and when to take it.
- Your doctor may change your dose if needed.
- Memantine HCl can be taken with food or without food.
- Do not use any tablets of Memantine HCl that are damaged or show signs of tampering.
- If you forget to take one dose of Memantine HCl, do not double up on the next dose. You should take only the next dose as scheduled.
- If you have forgotten to take Memantine HCl for several days, you should not take the next dose until you talk to your doctor.
- If you take too much Memantine HCl, call your doctor or poison control center at 1-800-222-1222 right away, or go to the nearest hospital emergency room.

What are the possible side effects of Memantine HCl?

Memantine HCl may cause side effects, including:

The most common side effects of Memantine HCl include:

- dizziness
- headache
- confusion
- constipation

These are not all the possible side effects of Memantine HCl. For more information, ask your doctor or pharmacist.

Call your doctor for medical advice about side effects. You may report side effects to FDA at 1-800-FDA-1088.

How should I store Memantine HCl?

- Store Memantine HCl at room temperature between 59°F to 77°F (15°C to 30°C).

What are the ingredients in Memantine HCl?

Memantine HCl tablets:

Active ingredients: memantine hydrochloride

Inactive ingredients: microcrystalline cellulose/colloidal silicon dioxide, talc, croscarmellose sodium, and magnesium stearate

Inactive ingredients of tablet film coating: hypromellose, titanium dioxide, polyethylene glycol 400, FD&C yellow #6 and FD&C blue #2 (5 mg tablets), and hypromellose, titanium dioxide, macrogol/polyethylene glycol 400 and iron oxide black (10 mg tablets)

Memantine HCl oral solution:

Active ingredients: memantine hydrochloride

Inactive ingredients: sorbitol solution (70%), methyl paraben, propylparaben, propylene glycol, glycerin, natural peppermint flavor #104, citric acid, sodium citrate, and purified water

Keep Memantine HCl and all medicines out of the reach of children.

General information about the safe and effective use of Memantine HCl.

Medicines are sometimes prescribed for purposes other than those listed in a Patient Information leaflet. Do not take Memantine HCl for a condition for which it was not prescribed. Do not give Memantine HCl to other people, even if they have the same condition. It may harm them.

This Patient Information leaflet summarizes the most important information about Memantine HCl. If you would like more information, talk with your doctor. You can ask your doctor or pharmacist for information about Memantine HCl that was written for healthcare professionals.

For more information about Memantine HCl call Actavis at 1-800-272-5525.

INSTRUCTIONS FOR USE

Memantine hydrochloride
Oral Solution

Directions for Using your Memantine HCl Oral Solution

Read these instructions before taking Memantine HCl Oral Solution and each time you get a refill. There may be new information. This information does not take the place of talking to your doctor about your medical condition or your treatment.

Preparing your dose of Memantine HCl Oral Solution.

You will need the following supplies:

1. Memantine HCl Oral Solution bottle with Child-resistant cap
2. Green syringe adaptor cap with lid
3. Oral dosing syringe
4. Plastic tube (in plastic bag)
5. Prescribing Information

1. Remove the oral dosing syringe, the green syringe adaptor cap, and remove the plastic tube from its protective plastic bag. Attach the tube to the green syringe adaptor cap if it is not already attached.

2. The bottle comes with a child-resistant cap. To remove the cap, you should push down on the cap and at the same time; turn the cap counter-clockwise (to the left).

3. Carefully remove the seal from the bottle and throw away.

4. Insert the green syringe adaptor cap, with the attached tube, all the way into the bottle and tightly screw the cap onto the bottle by turning the cap clockwise (to the right).

5. The green syringe adaptor cap has an opening with an attached lid. The adaptor is used to withdraw the correct dose of medicine from the bottle with the syringe. The attached adaptor lid should be closed in between doses.

6. Keep the bottle upright on a table. Open the syringe adaptor lid and insert the tip of syringe into the syringe adaptor opening.

- Make sure the syringe is pushed firmly into the adaptor opening.

7. While holding the syringe in place, gently pull the plunger of the syringe until you get to the correct mL (amount) of medicine you need.

- Do not worry about a few tiny bubbles. This will not affect your dose.

8. Remove the syringe from the syringe adaptor cap.

9. Remove the syringe from the bottle and slowly squirt the Memantine HCl Oral Solution into the corner of you or the patient's mouth. Do not mix Memantine HCl Oral Solution with any other liquid.

10. After use, reseal the bottle by snapping the attached syringe adaptor lid closed.

11. Rinse the empty syringe by inserting the open end of the syringe into a glass of water, pulling the plunger out to draw in water, and pushing the plunger in to remove the water. Repeat several times. Allow the syringe to air dry.

12. Store the bottle upright.

This Patient Information and Instructions for Use have been approved by the U.S. Food and Drug Administration.

Distributed by:
Actavis Pharma, Inc.
Parsippany, NJ 07054 USA

Manufactured by:
Forest Laboratories Ireland Ltd
Clonshaugh Business and Technology Park
Clonshaugh, Dublin 17, Ireland

Licensed from Merz Pharmaceuticals GmbH

© 2005-2015 Actavis

Revised April 2015

Repackaging Information

Please reference the How Supplied section listed above for a description of individual tablets. This drug product has been received by Aphena Pharma - TN in a manufacturer or distributor packaged configuration and repackaged in full compliance with all applicable cGMP regulations. The package configurations available from Aphena are listed below:

Count | 10 mg
3000 | 71610-011-18

Store between 20°-25°C (68°-77°F). See USP Controlled Room Temperature. Dispense in a tight light-resistant container as defined by USP. Keep this and all drugs out of the reach of children.

Repackaged by:
Cookeville, TN 38506
20171130JH

PRINCIPAL DISPLAY PANEL - 10mg

NDC 71610-011 - Memantine HCl 10mg - Rx Only